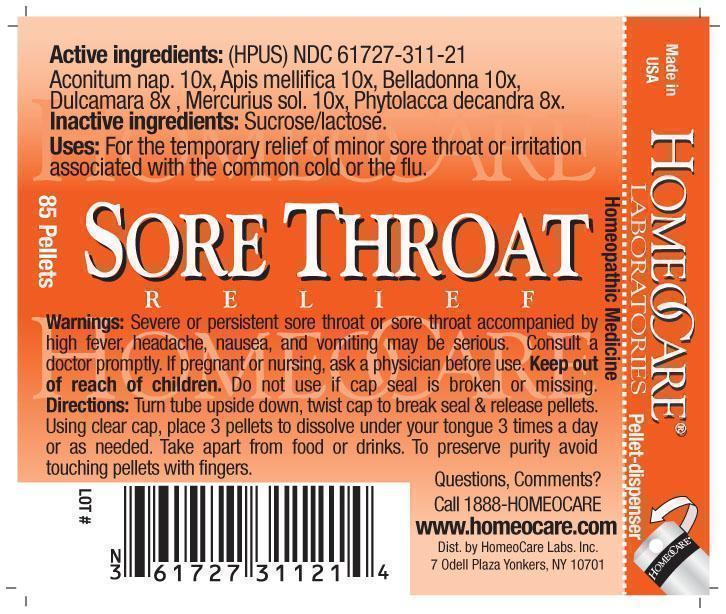 DRUG LABEL: Sore Throat Relief
NDC: 61727-311 | Form: PELLET
Manufacturer: Homeocare Laboratories
Category: homeopathic | Type: HUMAN OTC DRUG LABEL
Date: 20181226

ACTIVE INGREDIENTS: ACONITUM NAPELLUS 10 [hp_X]/4 g; APIS MELLIFERA 10 [hp_X]/4 g; ATROPA BELLADONNA 10 [hp_X]/4 g; SOLANUM DULCAMARA TOP 8 [hp_X]/4 g; MERCURIUS SOLUBILIS 10 [hp_X]/4 g; PHYTOLACCA AMERICANA ROOT 8 [hp_X]/4 g
INACTIVE INGREDIENTS: SUCROSE; LACTOSE

Sore Throat Relief

Active ingredients:

Aconitum nap. 10X, Apis mellifica 10X, Belladonna 10X, Dulcamara 8X, Mercurius sol. 10X, Phytolacca decandra 8X.

Inactive ingredients:

Sucrose/lactose.

Purpose:

For the temporary relief of minor sore throat or irritation associated with the common cold or the flu.

Keep out of reach of children.

Indications & Usage:

Turn tube upside down, twist cap to break seal & release pellets. Using clear cap, place 3 pellets to dissolve under your tongue 3 times a day or as needed. Take apart from food or drinks. To preserve purity avoid touching pellets with fingers.

Warnings:

Severe or persistent sore throat or sore throat accompanied by high fever, headache, nausea, and vomiting may be serious. Consult a doctor promptly. If pregnant or nursing, ask a physician before use. Keep out of reach of children. Do not use if cap seal is broken or missing.

Dosage & Administration:

Turn tube upside down, twist cap to break seal & release pellets. Using clear cap, place 3 pellets to dissolve under your tongue 3 times a day or as needed. Take apart from food or drinks. To preserve purity avoid touching pellets with fingers.

Sore Throat Relief

Homeopathic Medicine

85 Pellets

hcl_label_sthroat 2012.jpg